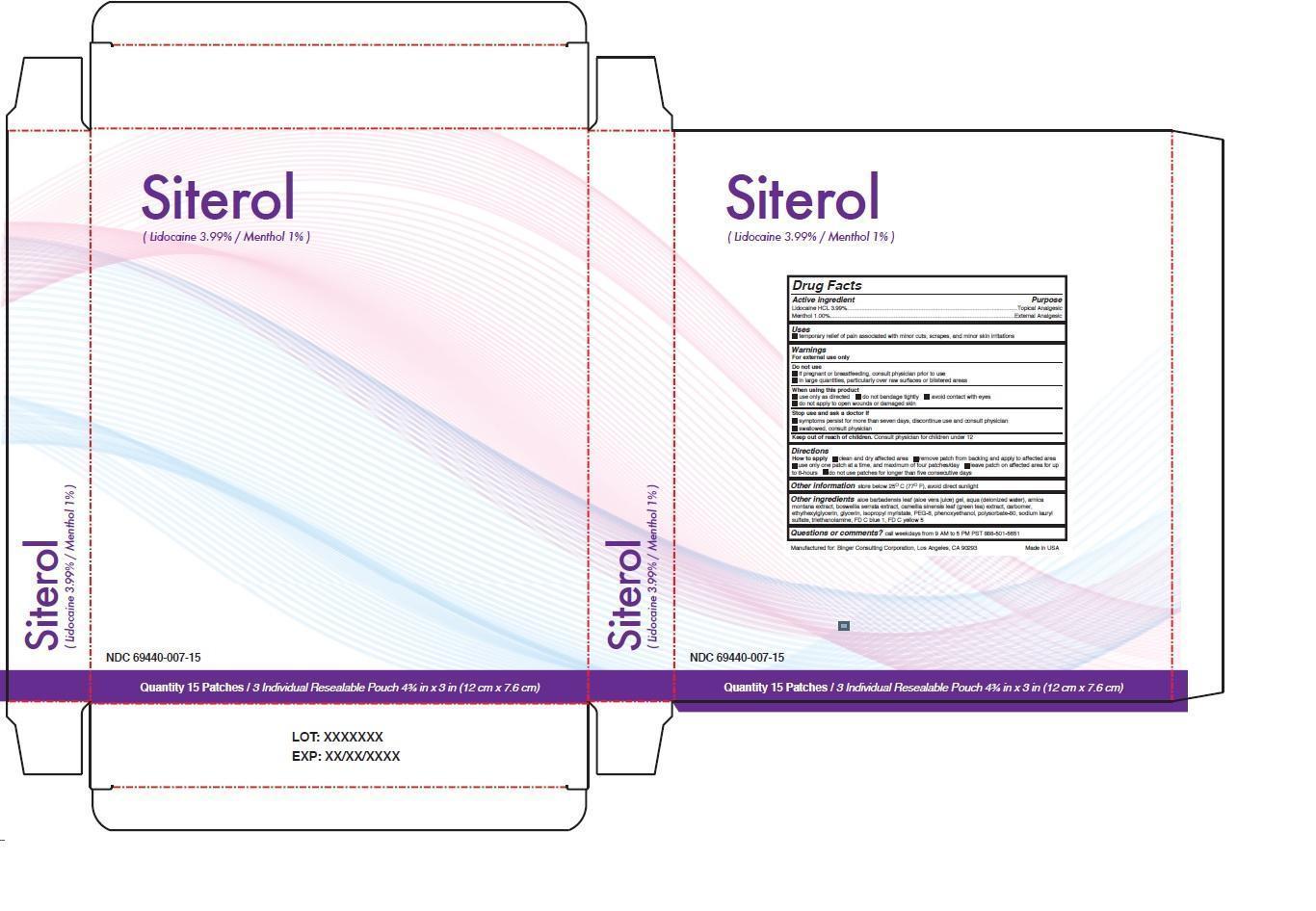 DRUG LABEL: Siterol
NDC: 69440-007 | Form: PATCH
Manufacturer: Binger Consulting Corporation
Category: otc | Type: HUMAN OTC DRUG LABEL
Date: 20241127

ACTIVE INGREDIENTS: LIDOCAINE HYDROCHLORIDE 3.99 g/100 g; MENTHOL, UNSPECIFIED FORM 1 g/100 g
INACTIVE INGREDIENTS: WATER; GLYCERIN; ARNICA MONTANA WHOLE; POLYSORBATE 80; ALOE VERA LEAF; BOSWELLIA SACRA WHOLE; GREEN TEA LEAF; CARBOMER COPOLYMER TYPE B (ALLYL PENTAERYTHRITOL CROSSLINKED); ETHYLHEXYLGLYCERIN; ISOPROPYL MYRISTATE; PEG-8 GLYCERYL ISOSTEARATE; PHENOXYETHANOL; SODIUM LAURYL SULFATE; TRIETHANOLAMINE BENZOATE; FD&C BLUE NO. 1; FD&C YELLOW NO. 5

Siterol

Active ingredient

Lidocaine HCL 3.99%

Menthol 1.00%

Purpose

Topical Analgesic

External Analgesic

Keep out of reach of children. Consult physician for children under 12.

Uses

• temporary relief of pain associated with minor cuts, scrapes, and minor skin irritations

Warnings

For external use only

Do not use

• if pregnant or breastfeeding, consult physician prior to use

• in large quantities, particularly over raw surfaces or blistered areas

When using this product

• use only as directed • do not bandage tightly • avoid contact with eyes

• do not apply to open wounds or damaged skin

Stop use and ask a doctor if

• symptoms persist for more than seven days, discontinue use and consult physician

• swallowed, consult physician

Directions

How to apply • clean and dry affected area • remove patch from backing and apply to affected area • use only one patch at a time, and maximum of four patches/day • leave patch on affected area for upto 8-hours • do not use patches for longer than five consecutive days

INACTIVE INGREDIENT

Other ingredients aloe barbadensis leaf (aloe vera juice) gel, aqua (deionized water), arnica montana extract, boswellia serrata extract, camellia sinensis leaf (green tea) extract, carbomer, ethylhexylglycerin, glycerin, isopropyl myristate, PEG-8, phenoxyethanol, polysorbate-80, sodium lauryl sulfate, triethanolamine, FD C blue 1, FD C yellow 5

Questions or comments? call weekdays from 9 AM to 5 PM PST 888-501-5651

Other information store below 25°C (77° F), avoid direct sunlight